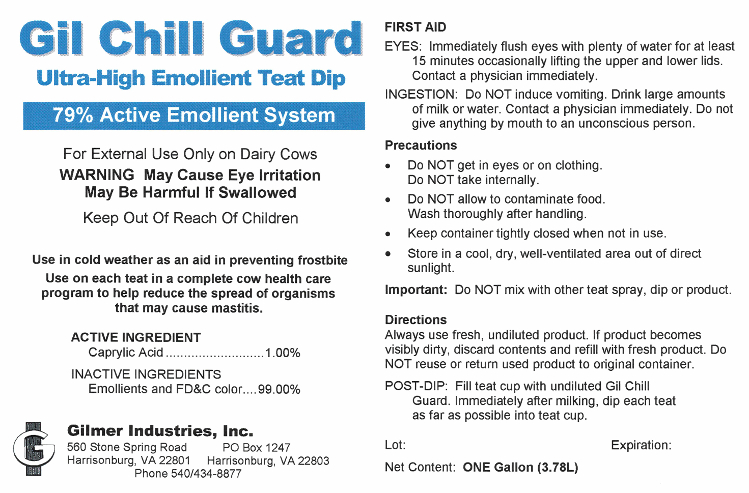 DRUG LABEL: Gil Chill Guard
NDC: 54420-018 | Form: LIQUID
Manufacturer: Gilmer Industries, Inc.
Category: animal | Type: OTC ANIMAL DRUG LABEL
Date: 20151228

ACTIVE INGREDIENTS: CAPRYLIC/CAPRIC ACID 10000 mg/1 L

Gil Chill Guard

PURPOSE

Ultra-High Emollient Teat Dip

79% Active EmollientSystem

Use in cold weather as an aid in preventing frostbite

Use on each teat in a complete cow health care program to help reduce the spread of organisms that may cause mastitis.

ACTIVE INGREDIENT

Caprylic Acid................................. 1.00%

INACTIVE INGREDIENTS

Emollients and FD&C color ......... 99.00%

USER SAFETY WARNINGS

For External Use Only on Dairy Cows

WARNING May Cause Eye Irritation
May Be Harmful If Swallowed

Keep Out Of Reach Of Children

PRECAUTIONS

- Do NOT get in eyes or on clothing.
- Do NOT take internally.Do NOT allow to contaminate food.
- Wash thoroughly after handling.Keep container tightly closed when not in use.
- Store in a cool, dry, well-ventilated area out of direct sunlight.

FIRST AID

EYES: Immediately flush eyes with plenty of water for at least
15 minutes occasionally lifting the upper and lower lids.
Contact a physician immediately.

INGESTION: Do NOT induce vomiting. Drink large amounts of milk or water. Contact a physician immediately. Do not give anything by mouth to an unconscious person.

DIRECTIONS

Important: Do NOT mix with other teat spray, dip or product.

Always use fresh, undiluted product. If product becomes visibly dirty, discard contents and refill with fresh product. Do NOT reuse or return used product to original container.

POST-DIP: Fill teat cup with undiluted Gil Chill Guard. Immediately after milking, dip each teat as far as possible into teat cup.